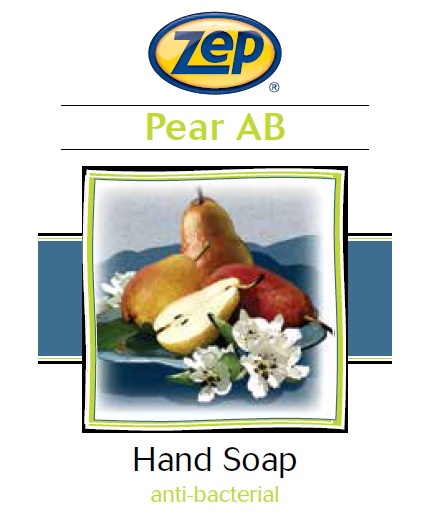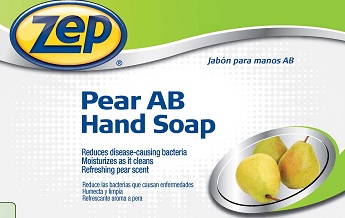 DRUG LABEL: ZEP PEAR AB HS
NDC: 66949-393 | Form: LIQUID
Manufacturer: Zep Inc.
Category: otc | Type: HUMAN OTC DRUG LABEL
Date: 20251226

ACTIVE INGREDIENTS: BENZALKONIUM CHLORIDE 0.13 g/100 mL
INACTIVE INGREDIENTS: METHYLISOTHIAZOLINONE; FD&C YELLOW NO. 5; METHYLCHLOROISOTHIAZOLINONE; PEG-120 METHYL GLUCOSE DIOLEATE; ANHYDROUS CITRIC ACID; COCO DIISOPROPANOLAMIDE; WATER; CETRIMONIUM CHLORIDE; LAUROYL/MYRISTOYL AMIDOPROPYL AMINE OXIDE; GLYCERIN; SODIUM CHLORIDE; EDETATE SODIUM; FD&C RED NO. 4

66949-393 / 3339 Pear AB

Active Ingredient

Benzalkonium Chloride 0.13%

Purpose

Antiseptic Handwash

Uses

For hand washing to decrease bacteria on skin.

Warnings

For external use only.

Do not use in the eyes; if in eyes, rinse promptly and thoroughly with water.

When using this product

- Do not swallow.
- If swallowed, do not induce vomiting and if individual is conscious, give large quantities of water to drink and consult a physician immediately.

Stop use and ask doctor if skin irritation or redness persists for more than 72 hours.

Keep out of reach of children and pets. Children must be supervised in use of this product.

Directions

- Wet hands with water.
- Press pump to dispense product into hands.
- Massage soap into hands and wrists, emphasizing back of hands, knuckles and cuticles.
- Rinse hands thoroughly and dry.

Other information

- Store at 20 to 25°C (68 to 77°F).
- Do not freeze.
- Dispose in accordance with all applicable federal, state and local regulations.

Inactive Ingredients

Water, Cetrimonium Chloride, Lauryl/Myristyl Amidopropyl Amine Oxide, Glycerin, Cocamide DIPA, PEG-120 Methyl Glucose Dioleate, Sodium Chloride, Fragrance, Citric Acid, Methylchloroisothiazolinone, Methylisothiazolinone, Tetrasodium EDTA, Red 4, Yellow 5

Questions or comments?

Call 1-877-I-BUY-ZEP (1-877-428-9937)